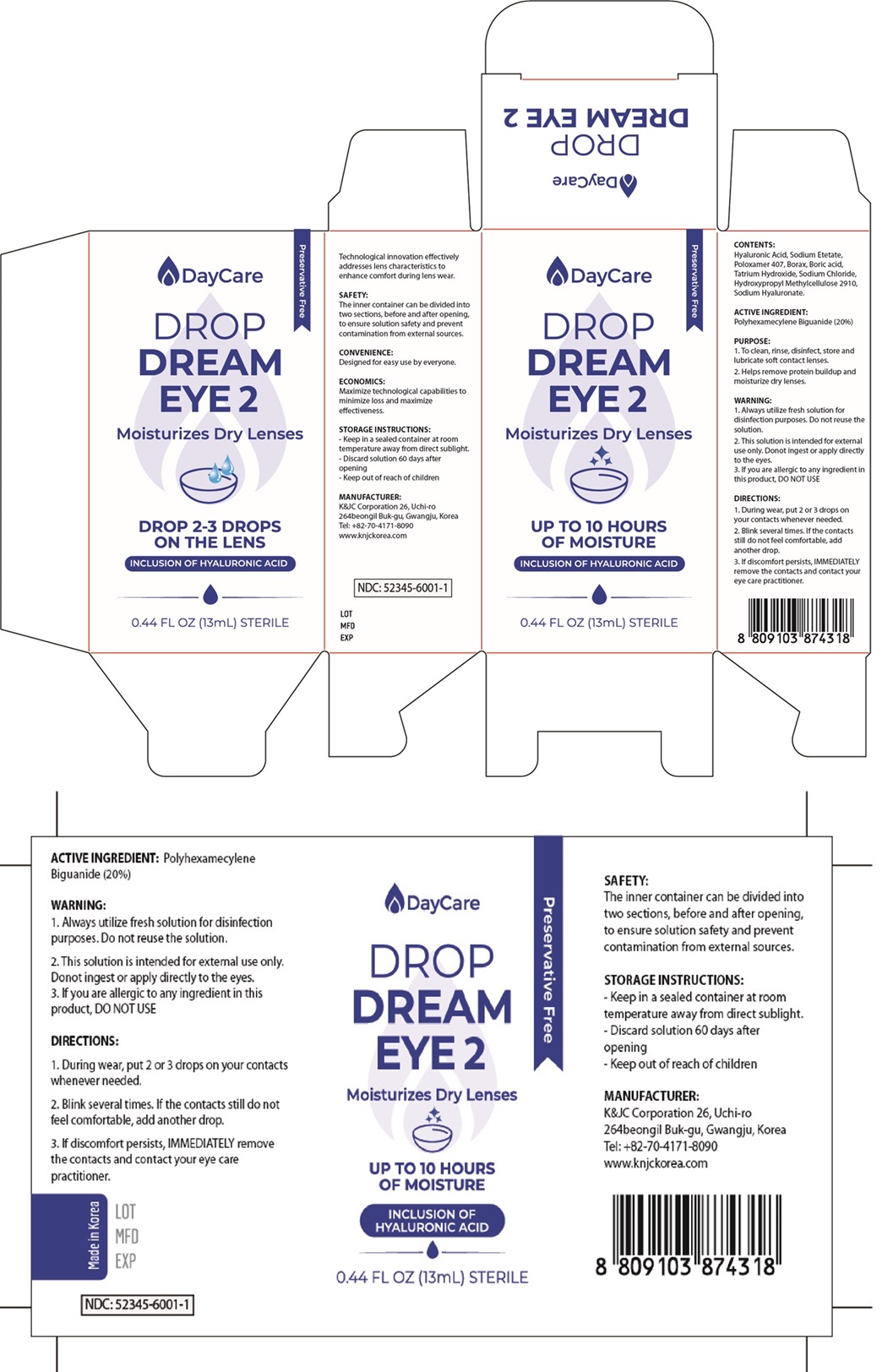 DRUG LABEL: Drop Dream Eye 2
NDC: 52345-6001 | Form: LIQUID
Manufacturer: K&J.C Co., Ltd
Category: otc | Type: HUMAN OTC DRUG LABEL
Date: 20240528

ACTIVE INGREDIENTS: POLYAMINOPROPYL BIGUANIDE 0.001 mg/100 mL
INACTIVE INGREDIENTS: WATER

Drug Facts

ACTIVE INGREDIENT

polyhexamethylene biguanide

INACTIVE INGREDIENT

poloxamer407, borax, oric acid, sodium hyaluronate, water, etc

PURPOSE

cleanses, rinses, disinfects, stores, lubricates and removed protein buildup

keep out of reach of the children

INDICATIONS AND USAGE

always use fresh solution to disinfacts, to not reuse solution

WARNINGS

keep in room temperature

DOSAGE AND ADMINISTRATION

opthalmic use only